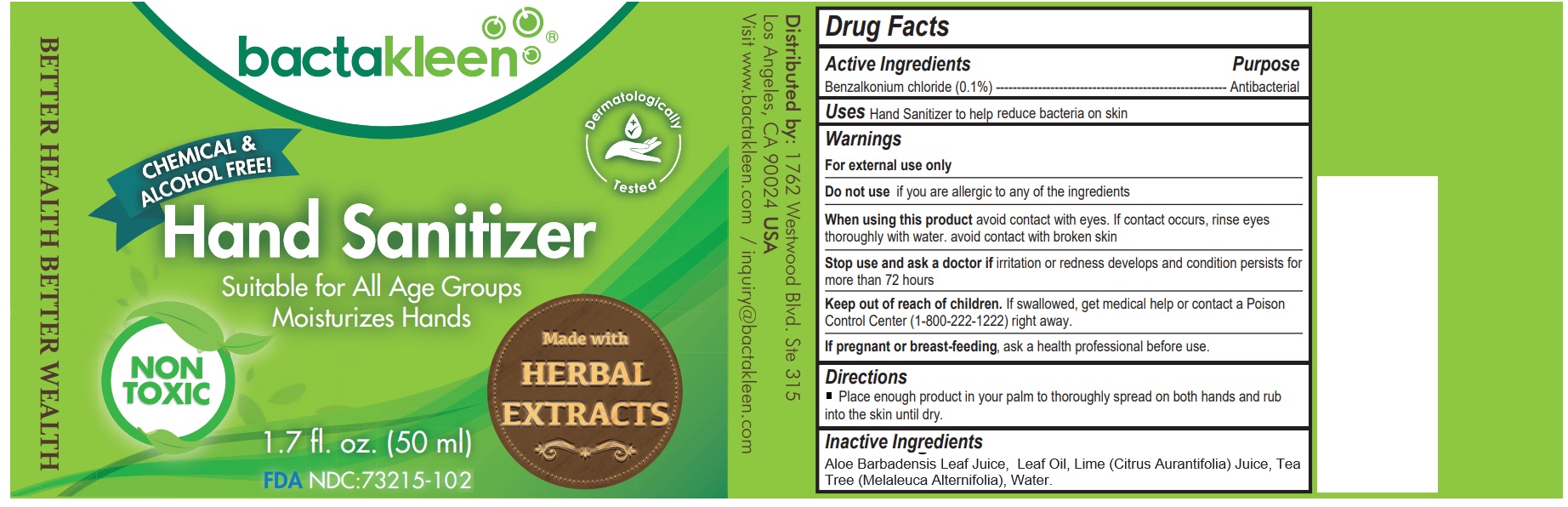 DRUG LABEL: BACTAKLEEN HAND SANITIZER
NDC: 73215-102 | Form: LIQUID
Manufacturer: Excelsia Technologies Sdn Bhd
Category: otc | Type: HUMAN OTC DRUG LABEL
Date: 20190807

ACTIVE INGREDIENTS: BENZALKONIUM CHLORIDE 0.05 g/50 mL
INACTIVE INGREDIENTS: WATER

BACTAKLEEN HAND SANITIZER

Active Ingredients

Benzalkonium chloride (0.1%)

Purpose

Antibacterial

Keep out of reach of children

If swallowed, get medical help or contact a Poison Control Center (1-800-222-1222) right away.

Uses

Hand Sanitizer to help reduce bacteria on skin

Warnings

For external use only

Do not use if you are allergic to any of the ingredients

When using this product avoid contact with eyes. If contact occurs, rinse eyes thoroughly with water. avoid contact with broken skin

Stop use and ask a doctor if irritation or redness develops and condition persists for more than 72 hours

If pregnant or breast-feeding, ask a health professional before use.

DOSAGE AND ADMINISTRATION

Place enough product in your palm to thoroughly spread on both hands and rub into the skin until dry.

Inactive Ingredients

Aloe Barbadensis Leaf Juice, Leaf Oil, Lime (Citrus Aurantifolia) Juice, Tea Tree (Melaleuca Alternifolia), Water.